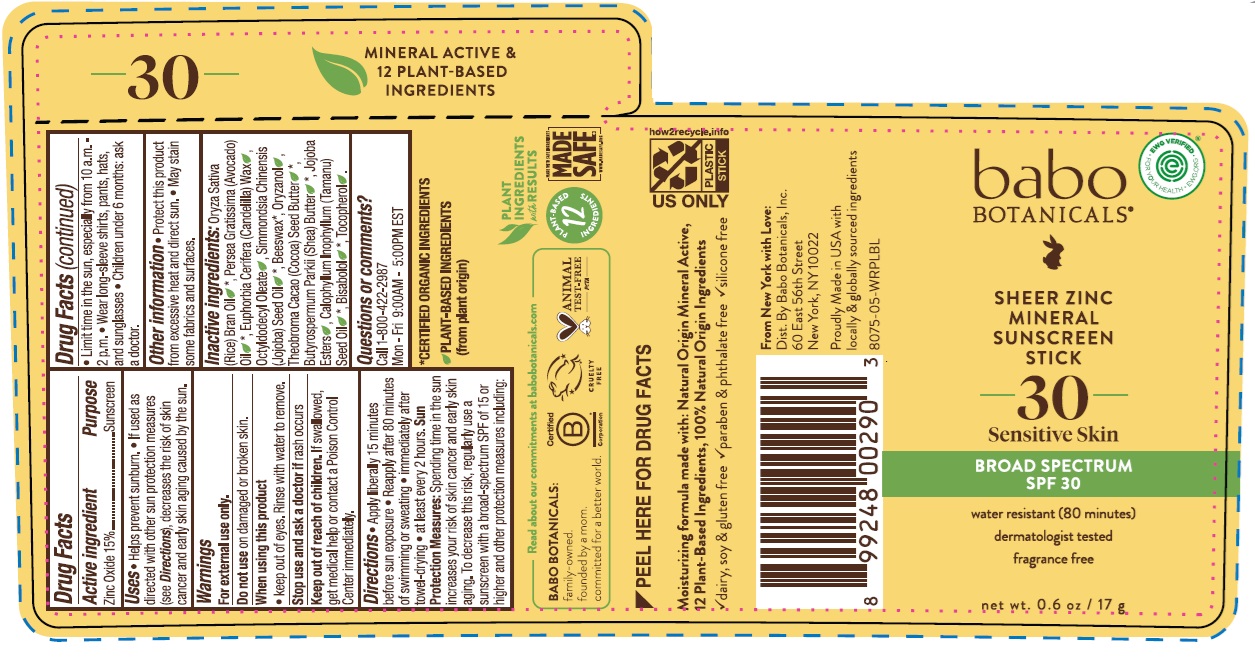 DRUG LABEL: Babo Botanicals Sheer Zinc Mineral Sunscreen SPF 30
NDC: 79265-5708 | Form: STICK
Manufacturer: Babo Botanicals, Inc.
Category: otc | Type: HUMAN OTC DRUG LABEL
Date: 20241218

ACTIVE INGREDIENTS: ZINC OXIDE 150 mg/1 g
INACTIVE INGREDIENTS: JOJOBA OIL, RANDOMIZED; JOJOBA OIL; COCOA BUTTER; TOCOPHEROL; AVOCADO OIL; RICE BRAN OIL; CANDELILLA WAX; OCTYLDODECYL OLEATE; SHEA BUTTER; CALOPHYLLUM TACAMAHACA SEED OIL; BEESWAX; LEVOMENOL; ORYZANOL

Babo Botanicals Sheer Zinc Mineral Sunscreen Stick SPF 30

Active ingredient

Zinc Oxide 15%

Purpose

Sunscreen

Uses

- Helps prevent sunburn
- If used as directed with other sun protection measures (see Directions), decreases the risk of skin cancer and early skin aging caused by the sun.

Warnings

For external use only

Do not use

on damaged or broken skin

When using this product

keep out of eyes. Rinse with water to remove

Stop use and ask doctor

if rash occurs

Keep out of reach of children.

If swallowed, get medical help or contact a Poison Control center right away.

Directions

- Apply liberally 15 minutes before sun exposure.
- Reapply after 80 minutes of swimming or sweating
- immediately after towel-drying
- at least every 2 hours.

Sun Protection Measures: Spending time in the sun increases your risk of skin cancer and early skin aging. To decrease this risk, regularly use a sunscreen with a broad-spectrum SPF of 15 or higher and other protection measures including:

- Limit time in the sun, especially from 10 a.m. - 2 p.m,
- Wear long-sleeve shirts, pants, hats and sunglasses
- Children under 6 months: ask a doctor

Other information

- Protect this product from excessive heat and direct sun.
- May stain some fabrics and surfaces.

Inactive ingredients

Oryza Sativa (Rice) Bran Oil*, Persea Gratissima (Avocado) Oil*, Euphorbia Cerifera (Candelilla) Wax, Octyldodecyl Oleate, Simmondsia Chinensis (Jojoba) Seed Oil*, Beeswax*, Oryzanol, Theobroma Cacao (Cocoa) Seed Butter*, Butyrospermum Parkii (Shea) Butter*, Jojoba Esters, Calophyllum Inophyllum (Tamanu) Seed Oil*, Bisabolol*, Tocopherol.

*CERTIFIED ORGANIC INGREDIENTS

Questions or comments?

Call 1-800-422-2987 M-F 9:00AM-5:00PM EST